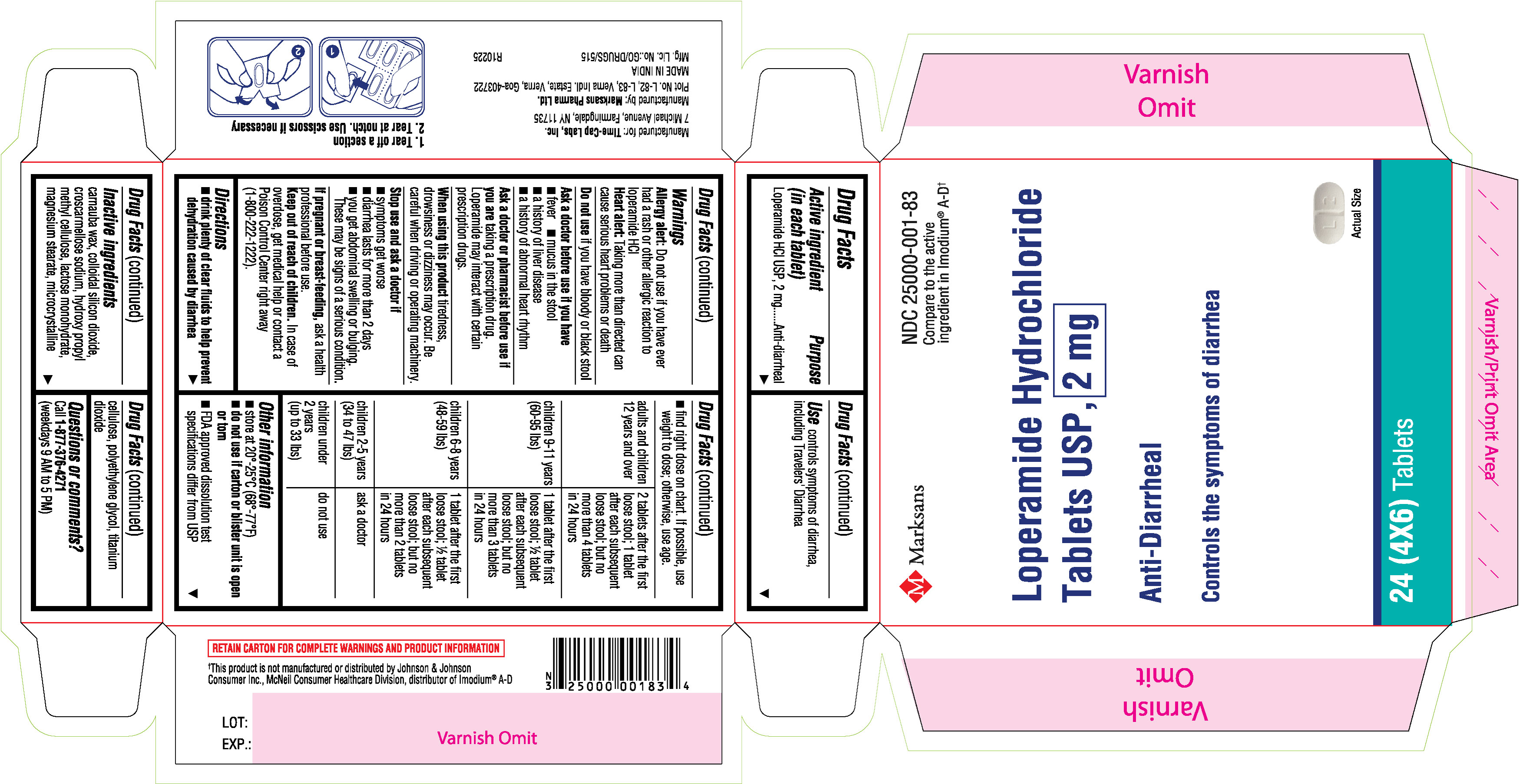 DRUG LABEL: Loperamide Hydrochloride 2mg
NDC: 25000-001 | Form: TABLET
Manufacturer: MARKSANS PHARMA LIMITED
Category: otc | Type: Human OTC Drug Label
Date: 20251119

ACTIVE INGREDIENTS: Loperamide Hydrochloride 2 mg/1 1
INACTIVE INGREDIENTS: carnauba wax; SILICON DIOXIDE; croscarmellose sodium; HYDROXYPROPYL METHYLCELLULOSE; lactose monohydrate; magnesium stearate; microcrystalline cellulose; polyethylene glycol; titanium dioxide

Loperamide Hydrochloride Tablets USP, 2mg

ACTIVE INGREDIENT(S)

Active ingredient (in each tablet)
Loperamide HCl USP, 2 mg

PURPOSE

Anti-diarrheal

USE(S)

Use controls symptoms of diarrhea, including Travelers' Diarrhea

WARNINGS

Allergy alert: Do not use if you have ever had a rash or other allergic reaction to loperamide HCl
Heart alert: Taking more than directed can cause serious heart problems or death

Do not use if you have bloody or black stool

Ask a doctor before use if you have
• fever
• mucus in the stool
• a history of liver disease
• a history of abnormal heart rhythm

Ask a doctor or pharmacist before use if you are taking a prescription drug.
Loperamide may interact with certain prescription drugs.

When using this product tiredness, drowsiness or dizziness may occur. Be careful when driving or operating machinery.

STOP USE AND ASK DOCTOR IF

Stop use and ask a doctor if
• symptoms get worse
• diarrhea lasts for more than 2 days
• you get abdominal swelling or bulging.
These may be signs of a serious condition.

PREGNANCY/BREASTFEEDING

If pregnant or breast-feeding, ask a health professional before use.

Keep out of reach of children. In case of overdose, get medical help or contact a Poison Control Center right away (1-800-222-1222).

DIRECTIONS

• drink plenty of clear fluids to help prevent dehydration caused by diarrhea
• find right dose on chart. If possible, use weight to dose; otherwise, use age.

adults and children 12 years and over | 2 tablets after the first loose stool; 1 tablet after each subsequent loose stool; but no more than 4 tablets in 24 hours
children 9-11 years (60-95 lbs) | 1 tablet after the first loose stool; ½ tablet after each subsequent loose stool; but no more than 3 tablets in 24 hours
children 6-8 years (48-59 lbs) | 1 tablet after the first loose stool; ½ tablet after each subsequent loose stool; but no more than 2 tablets in 24 hours
children 2-5 years (34 to 47 lbs) | ask a doctor
children under 2 years (up to 33 lbs) | do not use

STORAGE

Other information
• store at 20°-25°C (68°-77°F)
• do not use if carton or blister unit is open or torn
• FDA approved dissolution test specifications differ from USP

INACTIVE INGREDIENTS

Inactive ingredients carnauba wax, colloidal silicon dioxide, croscarmellose sodium, hydroxy propyl methyl cellulose, lactose monohydrate, magnesium stearate, microcrystalline cellulose, polyethylene glycol, titanium dioxide.

Questions or comments? Call 1-877-376-4271 (weekdays 9 AM to 5 PM)

Manufactured for: Time-Cap Labs, Inc.

7 Michael Avenue, Farmingdale, NY 11735
Manufactured by: Marksans Pharma Ltd.
Plot No. L-82, L-83, Verna Indl. Estate, Verna, Goa-403722

MADE IN INDIA

PRINCIPAL DISPLAY PANEL

NDC: 25000-001-83

Loperamide Hydrochloride Tablets USP, 2mg
24's count blister carton